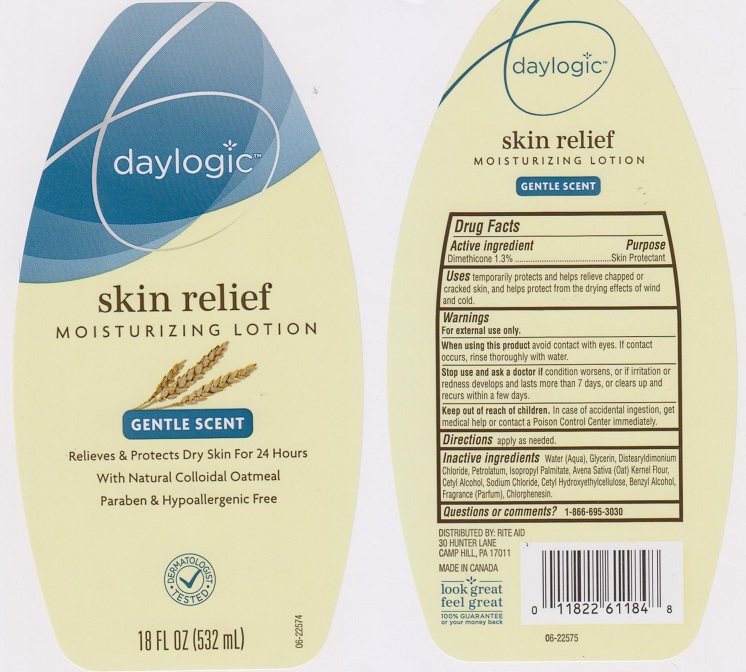 DRUG LABEL: Daylogic Skin Relief Moisturizing
NDC: 11822-3221 | Form: LOTION
Manufacturer: Rite Aid Corporation
Category: otc | Type: HUMAN OTC DRUG LABEL
Date: 20180209

ACTIVE INGREDIENTS: DIMETHICONE 13 mg/1 mL
INACTIVE INGREDIENTS: WATER; GLYCERIN; DISTEARYLDIMONIUM CHLORIDE; PETROLATUM; ISOPROPYL ALCOHOL; OAT; CETYL ALCOHOL; SODIUM CHLORIDE; CETYL HYDROXYETHYLCELLULOSE (550000 MW); BENZYL ALCOHOL; CHLORPHENESIN

Drug Facts

Active ingredient

Dimethicone 1.3%

Purpose

Skin Protectant

Uses

temporarily protects and helps relieve chapped or cracked skin, and helps protect from the drying effects of wind and cold.

Warnings

For external use only.

When using this product

avoid contact with eyes. If contact occurs, rinse thoroughly with water.

Stop use and ask a doctor if

condition worsens, or if irritation or redness develops and lasts more than 7 days, or clears up and recurs within a few days.

Keep out of reach of children.

In case of accidental ingestion, get medical help or contact a Poison Control Center immediately.

Directions

apply as needed.

Inactive ingredients

Water (Aqua), Glycerin, Distearyldimonium Chloride, Petrolatum, Isopropyl Palmitate, Avena Sativa (Oat) Kernel Flour, Cetyl Alcohol, Sodium Chloride, Cetyl Hydroxyethylcellulose, Benzyl Alcohol, Fragrance (Parfum), Chlorphenesin.

Questions or comments?

1-866-695-3030